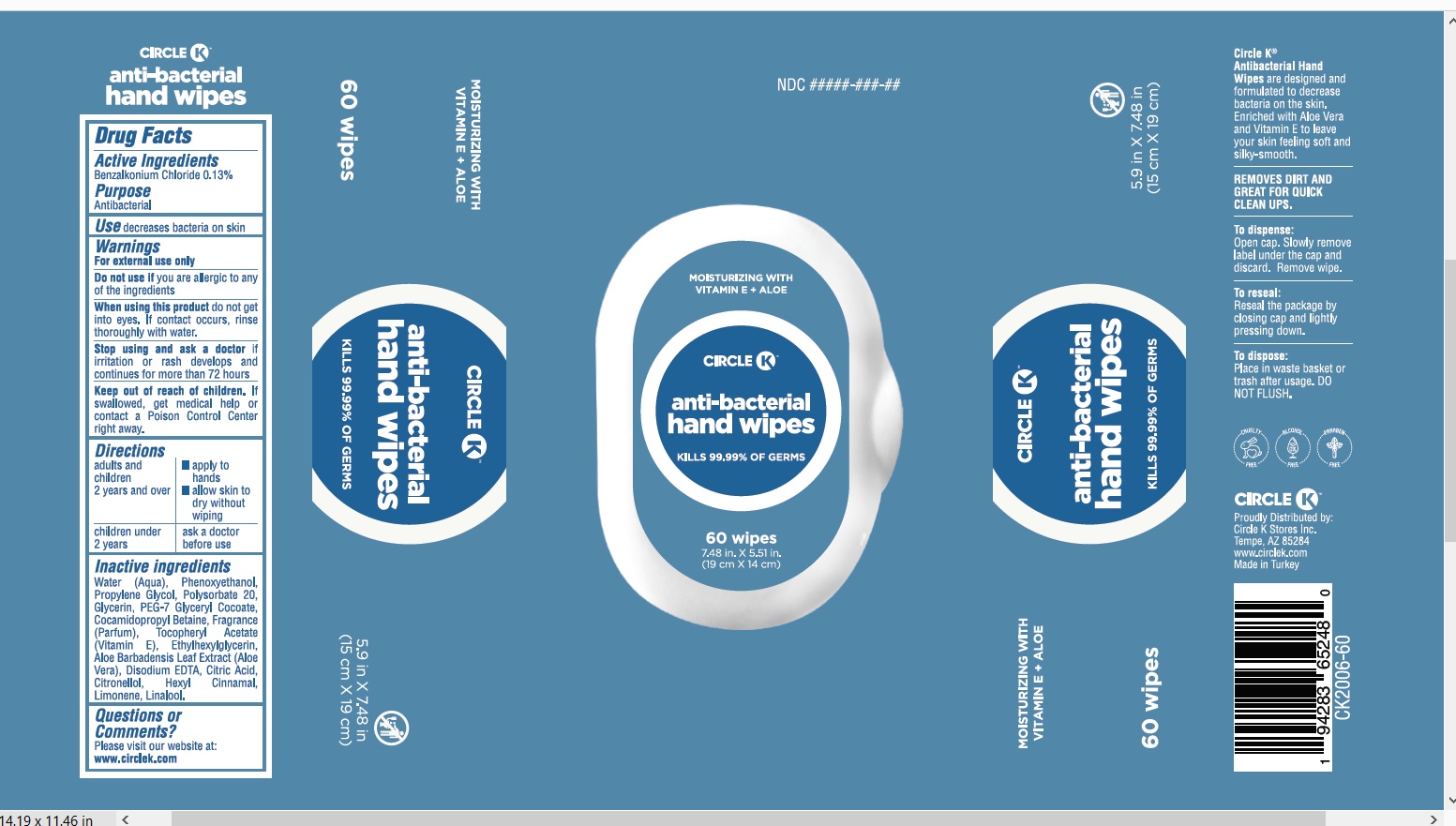 DRUG LABEL: Antibacterial Hand Wipes
NDC: 78711-002 | Form: CLOTH
Manufacturer: LIDERSAN SAGLIK VE GIDA URUNLERI ANONIM SIRKETI
Category: otc | Type: HUMAN OTC DRUG LABEL
Date: 20201101

ACTIVE INGREDIENTS: BENZALKONIUM CHLORIDE 0.0013 mg/100 mg
INACTIVE INGREDIENTS: WATER; GLYCERIN; PEG-7 GLYCERYL COCOATE; COCAMIDOPROPYL BETAINE; ALOE VERA LEAF; .ALPHA.-TOCOPHEROL ACETATE; POLYSORBATE 20; EDETATE SODIUM; PHENOXYETHANOL; LIMONENE, (+)-; ETHYLHEXYLGLYCERIN; POTASSIUM SORBATE; .ALPHA.-HEXYLCINNAMALDEHYDE; CITRIC ACID MONOHYDRATE; PROPYLENE GLYCOL; LINALOOL, (+)-

Circle K Antibacterial Hand Wipe

Active ingredients

Benalkonium chloride (0.13%)

Purpose

Antibacterial

Use

decrease bacteria on skin

Warnings

For external use only

Do Not Use

if you are allergic to any of the ingredients

When using this product

donot get into eyes.

if contact occurs, rinse thoroughly with water.

Stop use and ask a doctor if

irritation or rash develops.

and continues for more than 72 hours

Keep out of reach of children.

If swallowed, get medical help or contact a Poison Control Center right away

Directions:

*adults and children 2 years and over

- apply to hands
- allow to dry without wiping

*children under 2 years

- ask a doctor before use

Inactive ingredients

Water, Phenoxyethanol, Polysorbate 20, Gycerin, PEG-7 Glyceryl Cocoate, Cocamidropropyl Betaine, Fragrance, Aloe barbadensis leaf juice, Tocopheryl Acetate, ,Disodium EDTA , Ethylparaben, Citric Acid, Citronellol,Hexyl Cinnamal,Limonene,Linalool, Ethylhexyglycerin

Adverse reactions

Questions or comments?

Visit our website at www.circlek.com